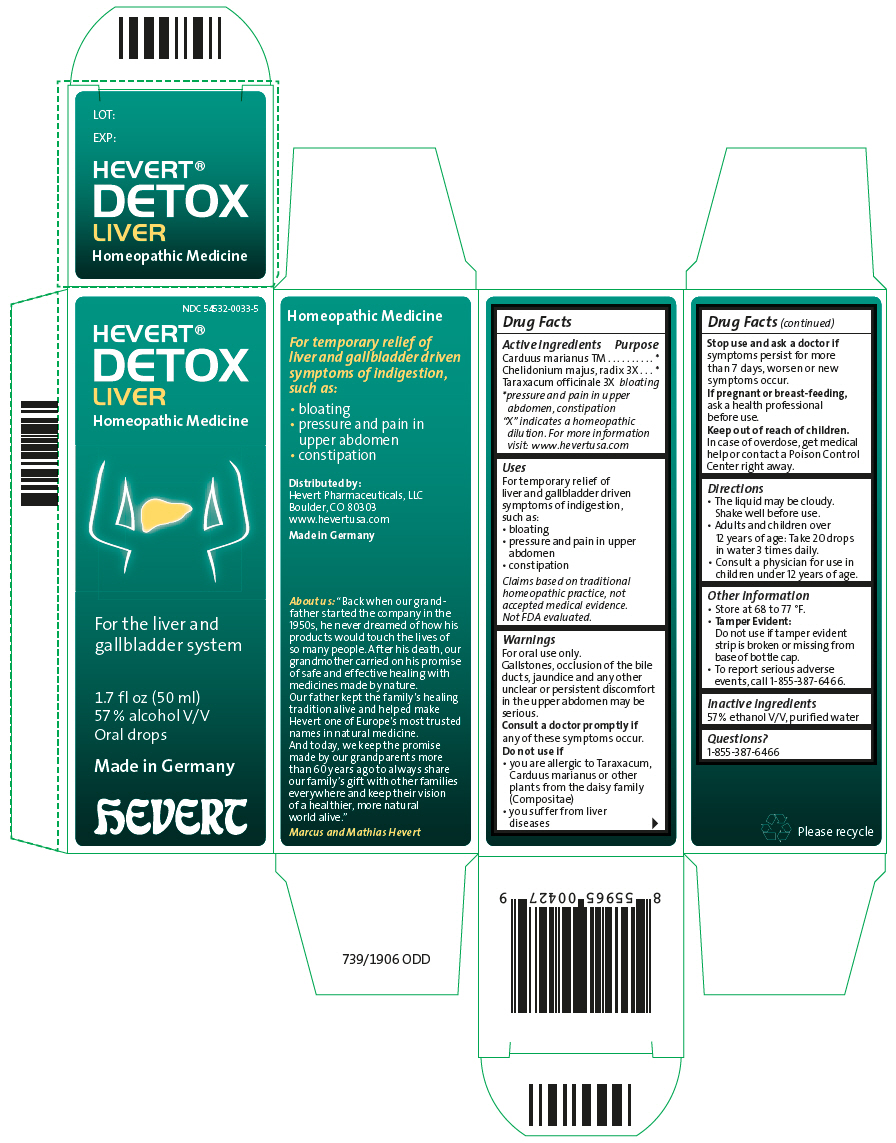 DRUG LABEL: Hevert Detox Liver
NDC: 54532-0033 | Form: LIQUID
Manufacturer: Hevert Arzneimittel GmbH & Co KG
Category: homeopathic | Type: HUMAN OTC DRUG LABEL
Date: 20221201

ACTIVE INGREDIENTS: Milk Thistle 1 [hp_X]/50 mL; Chelidonium Majus Root 3 [hp_X]/50 mL; Taraxacum officinale 3 [hp_X]/50 mL
INACTIVE INGREDIENTS: ALCOHOL; WATER

Hevert® Detox Liver

Drug Facts

ACTIVE INGREDIENT

Active ingredients | Purpose
Carduus marianus TM | [pressure and pain in upper abdomen, constipation]
Chelidonium majus, radix 3X
Taraxacum officinale 3X | bloating
"X" indicates a homeopathic dilution. For more information visit: www.hevertusa.com

Uses

For temporary relief of liver and gallbladder driven symptoms of indigestion, such as:

- bloating
- pressure and pain in upper abdomen
- constipation

Claims based on traditional homeopathic practice, not accepted medical evidence. Not FDA evaluated.

Warnings

For oral use only.

Gallstones, occlusion of the bile ducts, jaundice and any other unclear or persistent discomfort in the upper abdomen may be serious.

ASK DOCTOR

Consult a doctor promptly if any of these symptoms occur.

Do not use if

- you are allergic to Taraxacum, Carduus marianus or other plants from the daisy family (Compositae)
- you suffer from liver diseases

Stop use and ask a doctor if symptoms persist for more than 7 days, worsen or new symptoms occur.

PREGNANCY OR BREAST FEEDING

If pregnant or breast-feeding, ask a health professional before use.

Keep out of reach of children. In case of overdose, get medical help or contact a Poison Control Center right away..

Directions

- The liquid may be cloudy. Shake well before use.
- Adults and children over 12 years of age: Take 20 drops in water 3 times daily.
- Consult a physician for use in children under 12 years of age.

Other information

- Store at 68 to 77 °F.
- Tamper Evident:
  Do not use if tamper evident strip is broken or missing from base of bottle cap.
- To report serious adverse events, call 1-855-387-6466.

Inactive ingredients

57 % ethanol V/V, purified water

Questions?

1-855-387-6466

Distributed by:
Hevert Pharmaceuticals, LLC
Boulder, CO 80303

PRINCIPAL DISPLAY PANEL - 50 ml Bottle Carton

NDC 54532-0033-5

HEVERT®
DETOX
LIVER
Homeopathic Medicine

For the liver and
gallbladder system

1.7 fl oz (50 ml)
57 % alcohol V/V
Oral drops

Made in Germany

hEVERT